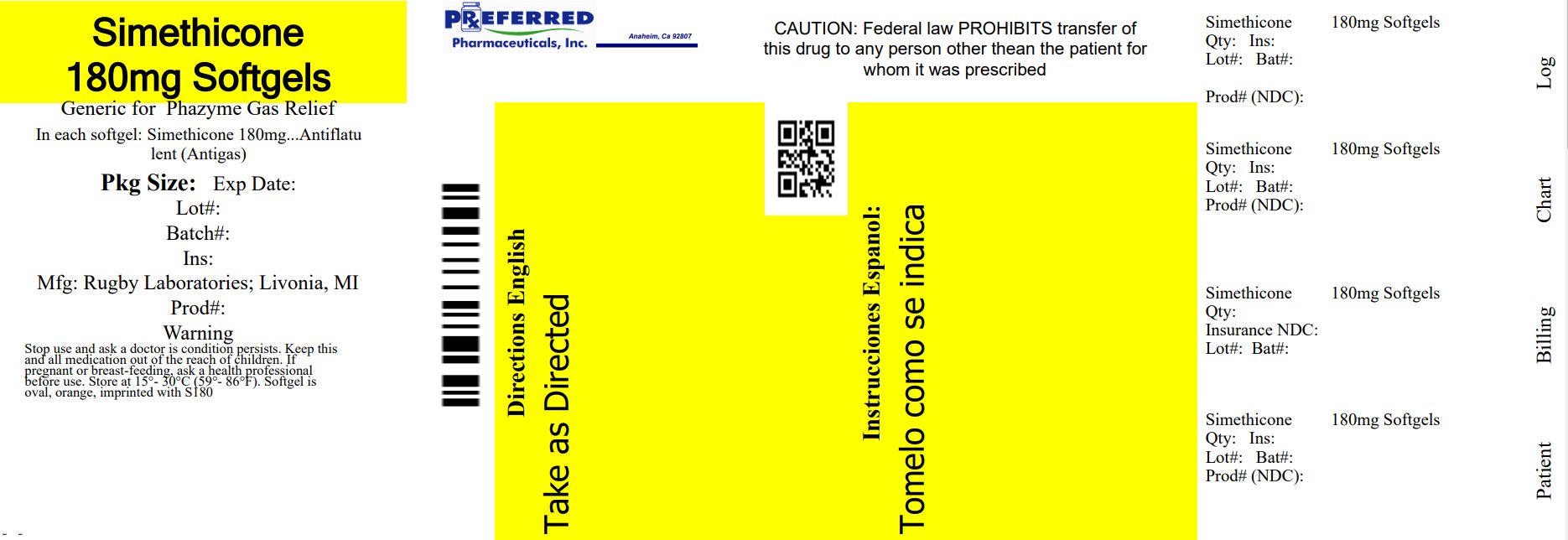 DRUG LABEL: Gas Relief
NDC: 68788-8785 | Form: CAPSULE, LIQUID FILLED
Manufacturer: Preferred Pharmaceuticals Inc.
Category: otc | Type: HUMAN OTC DRUG LABEL
Date: 20241212

ACTIVE INGREDIENTS: DIMETHICONE, UNSPECIFIED 180 mg/1 1
INACTIVE INGREDIENTS: GELATIN, UNSPECIFIED; GLYCERIN; FD&C RED NO. 40; WATER

Drug Facts

Active ingredient (in each softgel)

Simethicone 180 mg

Purpose

Antigas

Use

- relieves bloating, pressure, or fullness commonly referred to as gas

Warnings

Stop use and ask a doctor if

condition persists.

If pregnant or breast-feeding,

ask a health professional before use.

Directions

- swallow one or two softgels as symptoms occur
- do not exceed two softgels per 24 hours except under the advice and supervision of a physician

Other information

- store between 15-30ºC (59-86ºF)
- protect from heat and moisture

Inactive ingredients

FD&C yellow #6, gelatin, glycerin, water

Questions or comments?

Call 1-877-753-3935 Monday-Friday 9AM-5PM EST

Principal Display Panel

Compare to the active ingredient in Phazyme® Ultra Strength†

Ultra Strength

simethicone

Simethicone 180 mg

Antigas

fast relief of: gas, pressure, bloating & discomfort

Softgels

†This product is not manufactured or distributed by Prestige Consumer Healthcare, Inc., distributor of Phazyme® Ultra Strength.

TAMPER EVIDENT: DO NOT USE IF PRINTED SAFETY SEAL UNDER CAP IS BROKEN OR MISSING

Distributed by:

RUGBY® LABORATORIES

Indianapolis, IN 46268

Repackaged By: Preferred Pharmaceuticals Inc.

Product Label

RUGBY Gas Relief